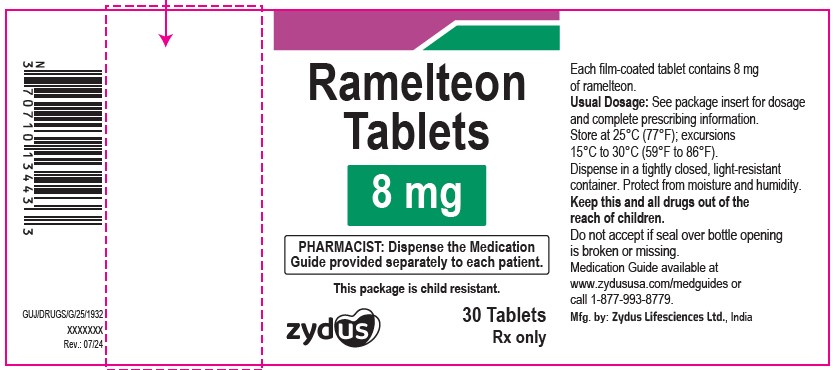 DRUG LABEL: Ramelteon
NDC: 70771-1495 | Form: TABLET
Manufacturer: Zydus Lifesciences Limited
Category: prescription | Type: HUMAN PRESCRIPTION DRUG LABEL
Date: 20241204

ACTIVE INGREDIENTS: RAMELTEON 8 mg/1 1
INACTIVE INGREDIENTS: ANHYDROUS LACTOSE; FERRIC OXIDE RED; FERRIC OXIDE YELLOW; FERROSOFERRIC OXIDE; HYPROMELLOSE 2910 (3 MPA.S); POLYETHYLENE GLYCOL 6000; POVIDONE; SILICON DIOXIDE; SODIUM STEARYL FUMARATE; STARCH, CORN; TITANIUM DIOXIDE

RAMELTEON TABLETS

PACKAGE LABEL.PRINCIPAL DISPLAY PANEL

NDC 70771-1495-3

Ramelteon Tablets, 8 mg

30 Tablets

Rx only